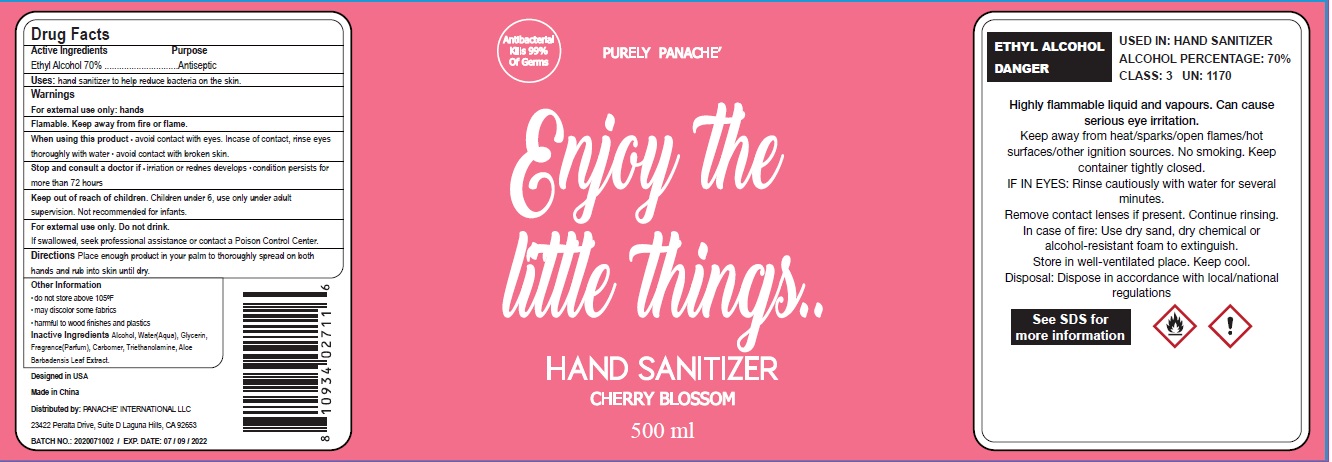 DRUG LABEL: Hand Sanitizer Cherry Blossom
NDC: 74511-007 | Form: LIQUID
Manufacturer: Xiamen Meidai Cross-border E-commerce Co., Ltd.
Category: otc | Type: HUMAN OTC DRUG LABEL
Date: 20200719

ACTIVE INGREDIENTS: alcohol 70 mL/100 mL
INACTIVE INGREDIENTS: WATER; ALOE VERA LEAF; GLYCERIN; TROLAMINE

Drug facts

ACTIVE INGREDIENT

Ethyl Alcohol .......... 70%

purpose

antiseptic

KEEP OUT OF REACH OF CHILDREN

Children under 6, use only under adult supervision. Not recommended for infants.

if swallowed, seek professional assistance or contact a Poison Control Center.

INDICATIONS AND USAGE

Hand sanitizer to help reduce bacteria on the skin.

WARNINGS

For external use only: hands
Flammable. Keep away from fire or flame.

When using this product, avoid contact with eyes. In case of contact, flush eyes thoroughly with water. Avoid contact with broken skin.

Stop and consult a doctor if irritation or redness develops. Condition persist for more than 72 hours.

Directions:

Place enough product in your palm tothoroughly spread on both hands and rub into skin until dry.

Other information:

- Do not store above 105℉
- May discolr some fabrics
- Harmful to wood finishes and plastics.

INACTIVE INGREDIENT

Water (Aqua), Glycerin Fragrance (Parfum), Carbomer, Triethanolamine, Aloe barbadensis Leaf Extract.